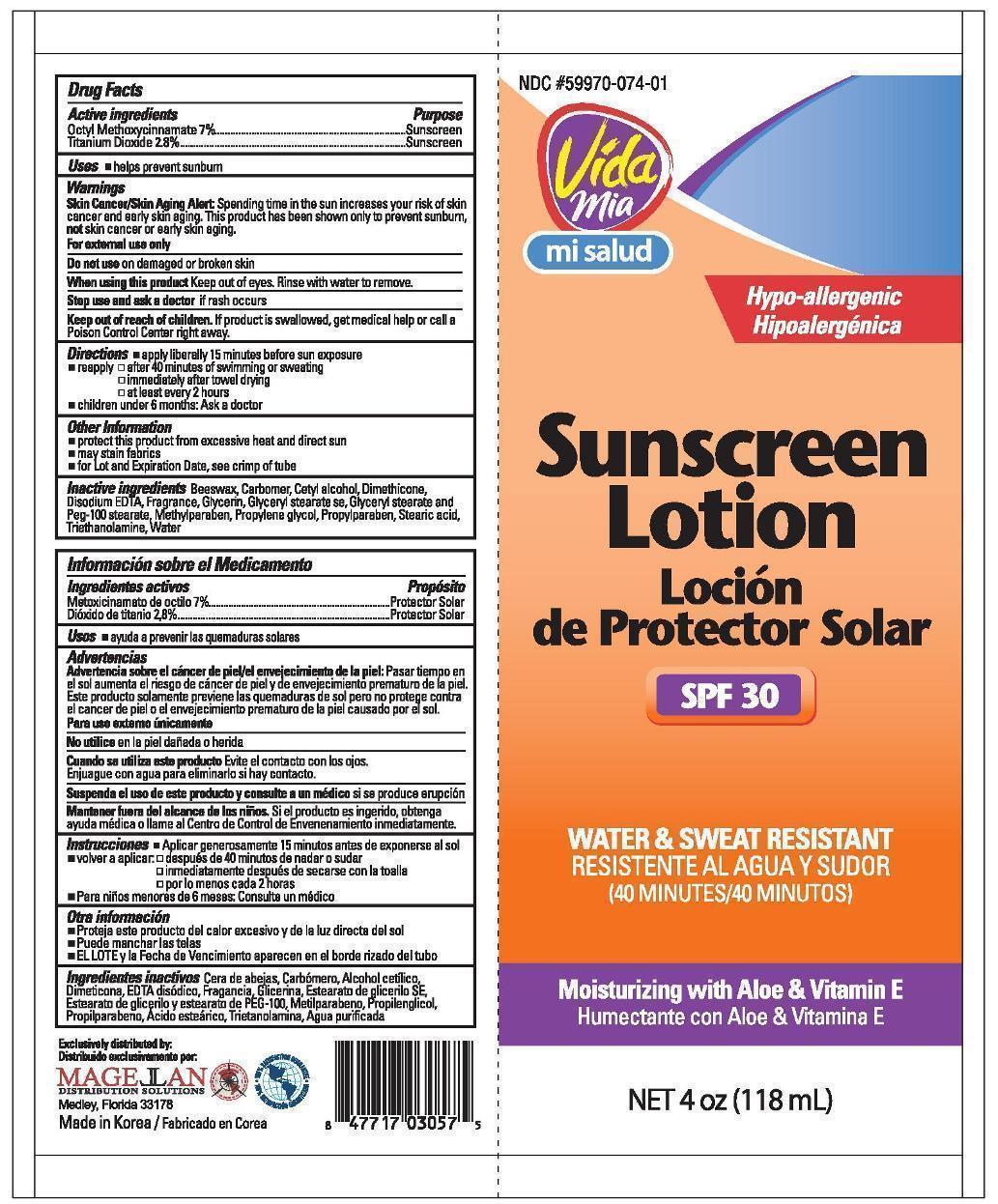 DRUG LABEL: Face and Body Sunscreen
NDC: 59970-074 | Form: LOTION
Manufacturer: Navarro Discount Pharmacies,LLC
Category: otc | Type: HUMAN OTC DRUG LABEL
Date: 20130122

ACTIVE INGREDIENTS: OCTINOXATE 7 mg/100 mg; TITANIUM DIOXIDE 2.8 mg/100 mg
INACTIVE INGREDIENTS: YELLOW WAX; CETYL ALCOHOL; DIMETHICONE; EDETATE DISODIUM; GLYCERIN; GLYCERYL MONOSTEARATE; PEG-100 STEARATE; METHYLPARABEN; PROPYLENE GLYCOL; PROPYLPARABEN; STEARIC ACID; TROLAMINE; WATER

Drug Facts

Active Ingredients

Octyl Methoxycinnamate 7%

Titanium Dioxide 2.8%

Purpose

Sunscreen

Sunscreen

Use

helps prevent sunburn

Warnings

Skin Cancer/Skin Aging Alert: Spending time in the sun increases your risk of skin cancer and early skin aging. This product has been shown only to prevent sunburn, not skin cancer or early skin aging.

For external use only

Do not use

on damaged or broken skin

When using this product

Keep out of eyes. Rinse with water to remove.

Stop use and ask a doctor

if rash occurs

Keep out of reach of children.

If product is swallowed, get medical help or call a Poison Control Center right away.

Directions

- apply liberally 15 minutes before sun exposure
- reapply:
-
  - after 40 minutes of swimming or sweating
  - immediately after towel drying
  - at least every 2 hours
- children under 6 months: Ask a doctor

Other information

- protect this product from excessive heat and direct sun
- may stain fabrics
- for Lot and Expiration Date, see crimp of tube

Inactive Ingredients

beeswax, carbomer, cetyl alcohol, dimethicone, disodium edta, fragrance, glycerin, glyceryl stearate se, glyceryl stearate and peg-100 stearate, methylparaben, propylene glycol, propylparaben, stearic acid, triethanolamine, water

Package label

Vida Mia Sunscreen Lotion